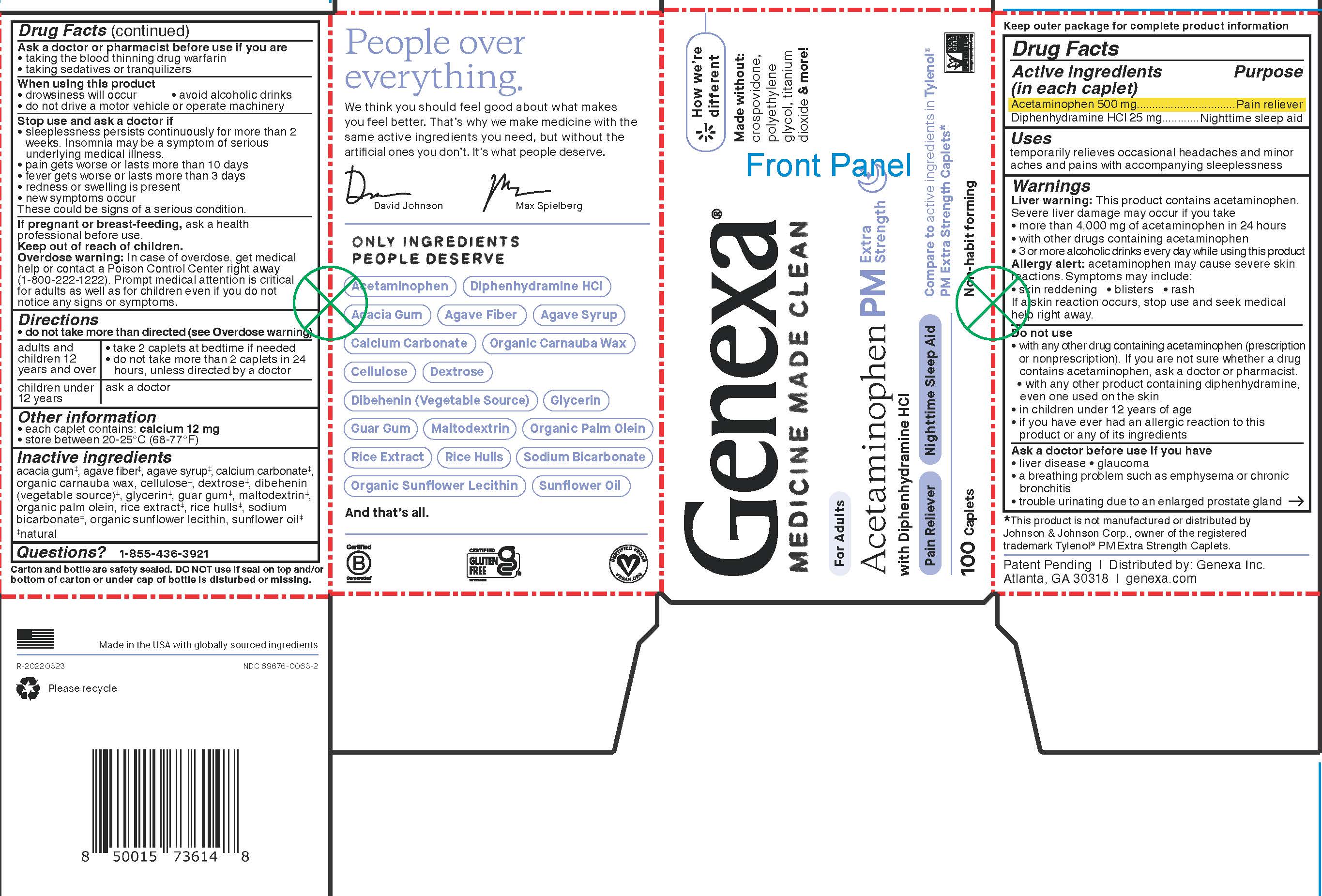 DRUG LABEL: Genexa Acetaminophen PM
NDC: 69676-0063 | Form: TABLET, COATED
Manufacturer: Genexa Inc.
Category: otc | Type: HUMAN OTC DRUG LABEL
Date: 20250220

ACTIVE INGREDIENTS: ACETAMINOPHEN 500 mg/1 1; DIPHENHYDRAMINE HYDROCHLORIDE 25 mg/1 1
INACTIVE INGREDIENTS: CALCIUM CARBONATE; RICE BRAN; POWDERED CELLULOSE; INULIN; PALM OIL; ACACIA; AGAVE TEQUILANA JUICE; CARNAUBA WAX; DEXTROSE; GUAR GUM; MALTODEXTRIN; SODIUM BICARBONATE; LECITHIN, SUNFLOWER; GLYCERYL DIBEHENATE; SUNFLOWER OIL; GLYCERIN

Acetaminophen PM Extra Strength Caplets

Drug Facts

Active ingredients (in each caplet)

Acetaminophen 500 mg

Diphenhydramine HCl 25 mg

Purpose

Pain reliever

Nighttime sleep aid

Uses

temporarily relieves occasional headaches and minor aches and pains with accompanying sleeplessness

Warnings

Liver warning: This product contains acetaminophen.

Severe liver damage may occur if you take

- more than 4,000 mg of acetaminophen in 24 hours
- with other drugs containing acetaminophen
- 3 or more alcoholic drinks every day while using this product

Allergy alert: acetaminophen may cause severe skin reactions. Symptoms may include:

- skin reddening
- blisters
- rash

If a skin reaction occurs, stop use and seek medical help right away.

Do not use

- with any other drug containing acetaminophen (prescription or nonprescription). If you are not sure whether a drug contains acetaminophen, ask a doctor or pharmacist.
- with any other product containing diphenhydramine, even one used on the skin
- in children under 12 years of age
- if you have ever had an allergic reaction to this product or any of its ingredients

Ask a doctor before use if you have

- liver disease
- glaucoma
- a breathing problem such as emphysema or chronic bronchitis
- trouble urinating due to an enlarged prostate gland

Ask a doctor or pharmacist before use if you are

- taking the blood thinning drug warfarin
- taking sedatives or tranquilizers

When using this product

- drowsiness will occur
- avoid alcoholic drinks
- do not drive a motor vehicle or operate machinery

Stop use and ask a doctor if

- sleeplessness persists continuously for more than 2 weeks. Insomnia may be a symptom of serious underlying medical illness.
- pain gets worse or lasts more than 10 days
- fever gets worse or lasts more than 3 days
- redness or swelling is present
- new symptoms occur

These could be signs of a serious condition.

PREGNANCY OR BREAST FEEDING

If pregnant or breast-feeding, ask a health professional before use.

Keep out of reach of children.

OVERDOSAGE

Overdose warning: In case of overdose, get medical help or contact a Poison Control Center right away (1-800-222-1222). Prompt medical attention is critical for adults as well as for children even if you do not notice any signs or symptoms.

Directions

• do not take more than directed (see Overdose warning)

adults and children 12 years and over | - take 2 caplets at bedtime if needed - do not take more than 2 caplets in 24 hours, unless directed by a doctor
children under 12 years | ask a doctor

Other information

- each caplet contains: calcium 12 mg
- store between 20-25°C (68-77°F)

Inactive ingredients

acacia gum‡, agave fiber‡, agave syrup‡, calcium carbonate‡, organic carnauba wax, cellulose‡, dextrose‡, dibehenin (vegetable source)‡, glycerin‡, guar gum‡, maltodextrin‡, organic palm olein, rice extract‡, rice hulls‡, sodium bicarbonate‡, organic sunflower lecithin, sunflower oil‡

‡natural

Questions? 1-855-436-3921

Carton and bottle are safety sealed. DO NOT use if seal on top and/or bottom of carton or under cap of bottle is disturbed or missing.

*This product is not manufactured or distributed by Johnson & Johnson Corp., owner of the registered trademark Tylenol® PM Extra Strength Caplets.

Patent Pending | Distributed by: Genexa Inc.

Atlanta, GA 30318 | genexa.com

Made in the USA with globally sourced ingredients

NDC 69676-0063-2

Directions

• do not take more than directed (see Overdose warning)

adults and children 12 years and over | - take 2 caplets at bedtime if needed - do not take more than 2 caplets in 24 hours, unless directed by a doctor
children under 12 years | ask a doctor

PACKAGE LABEL

Genexa®

MEDICINE MADE CLEAN

For Adults

Acetaminophen PM Extra Strength

with Diphenhydramine HCl

Pain Reliever Nighttime Sleep Aid

Compare to active ingredients in Tylenol® PM Extra Strength Caplets*

100 Caplets

Non-habit forming

How we're different

Made without: crospovidone, polyethylene glycol, titanium dioxide & more!